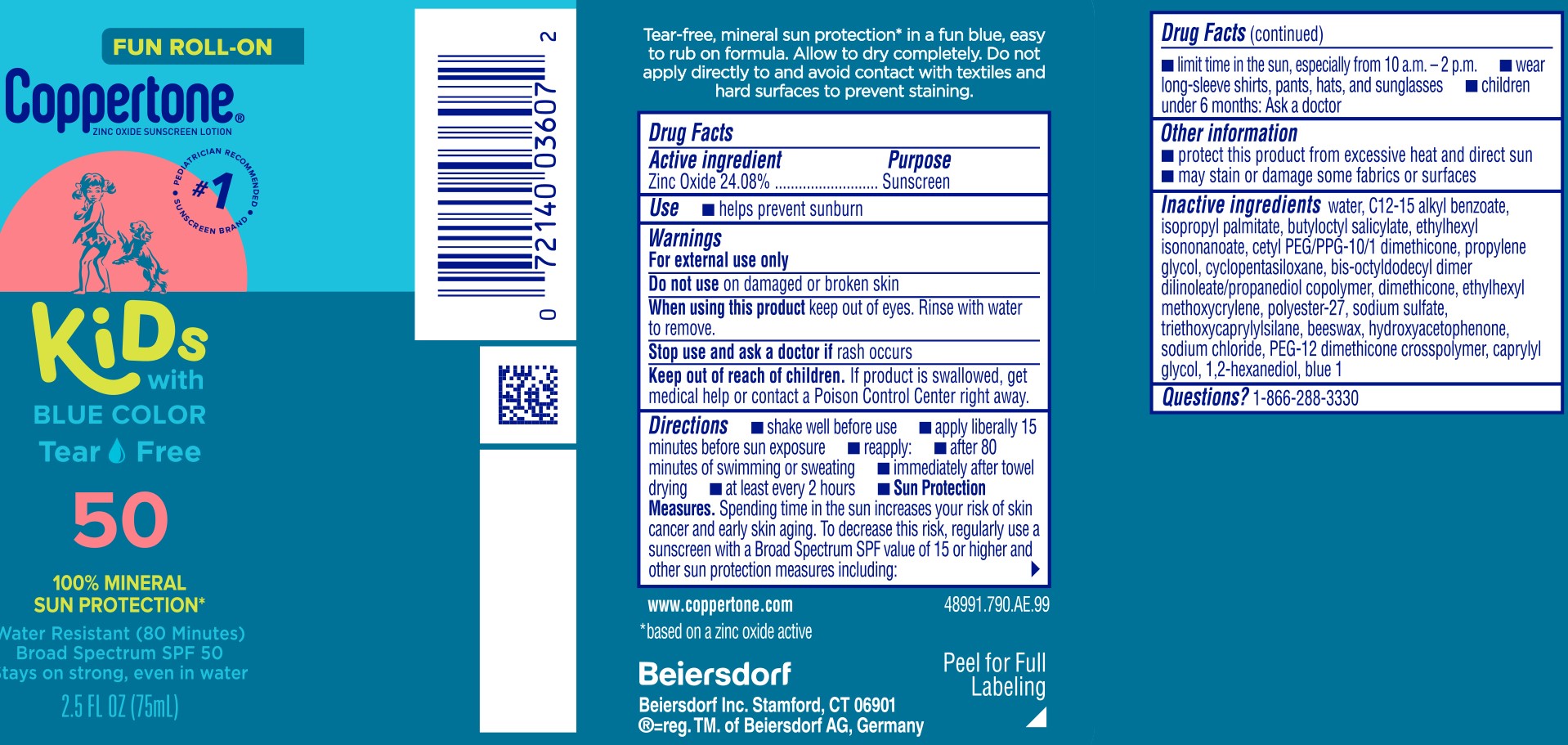 DRUG LABEL: Coppertone Kids Roll-On Sunscreen SPF 50
NDC: 66800-4026 | Form: LOTION
Manufacturer: Beiersdorf Inc
Category: otc | Type: HUMAN OTC DRUG LABEL
Date: 20251231

ACTIVE INGREDIENTS: ZINC OXIDE 24.08 g/100 g
INACTIVE INGREDIENTS: SODIUM SULFATE; PEG-12 DIMETHICONE; BASIC BLUE 1; WATER; BUTYLOCTYL SALICYLATE; CETYL PEG/PPG-10/1 DIMETHICONE (HLB 2); ETHYLHEXYL METHOXYCRYLENE; PROPYLENE GLYCOL; CYCLOMETHICONE 5; BIS-OCTYLDODECYL DIMER DILINOLEATE/PROPANEDIOL COPOLYMER; ISOPROPYL PALMITATE; ETHYLHEXYL ISONONANOATE; TRIETHOXYCAPRYLYLSILANE; HYDROXYACETOPHENONE; SODIUM CHLORIDE; CAPRYLYL GLYCOL; ALKYL (C12-15) BENZOATE; DIMETHICONE; POLYESTER-7; SYNTHETIC BEESWAX; 1,2-HEXANEDIOL

Kids Roll-On Lotion SPF 50

Active ingredient

Zinc Oxide 24.08%

Purpose

Sunscreen

Use

■ helps prevent sunburn

Warnings

For external use only

Do not useon damaged or broken skin

WHEN USING

When using this productkeep out of eyes. Rinse with water to remove.

Stop use and ask a doctor ifrash occurs

Keep out of reach of children.If product is swallowed, get medical help or contact a Poison Control Center right away.

Directions

■ shake well before use

■ apply liberally 15 minutes before sun exposure

■ reapply:

■ after 80 minutes of swimming or sweating

■ immediately after towel drying

■ at least every 2 hours

■ Sun Protection Measures.Spending time in the sun increases your risk of skin cancer and early skin aging. To decrease this risk, regularly use a sunscreen with a Broad Spectrum SPF value of 15 or higher and other sun protection measures including:

■ limit time in the sun, especially from 10 a.m. – 2 p.m.

■ wear long-sleeve shirts, pants, hats, and sunglasses

■ children under 6 months: Ask a doctor

Other information

■ protect this product from excessive heat and direct sun

■ may stain or damage some fabrics or surfaces

Inactive ingredients

water, C12-15 alkyl benzoate, isopropyl palmitate, butyloctyl salicylate, ethylhexyl isononanoate, cetyl PEG/PPG-10/1 dimethicone, propylene glycol, cyclopentasiloxane, bis-octyldodecyl dimer dilinoleate/propanediol copolymer, dimethicone, ethylhexyl methoxycrylene, polyester-27, sodium sulfate, triethoxycaprylylsilane, beeswax, hydroxyacetophenone, sodium chloride, PEG-12 dimethicone crosspolymer, caprylyl glycol, 1,2-hexanediol, blue 1

Questions?

1-866-288-3330

PACKAGE LABEL

Fun Roll-On

Coppertone®

Zinc Oxide Sunscreen Lotion

#1 Pediatrician Recommended Sunscreen Brand

Kids with Blue Color

Tear Free

50

100% Mineral Sun Protection*

Water Resistant (80 Minutes)

Broad Spectrum SPF 50

Stays on strong, even in water